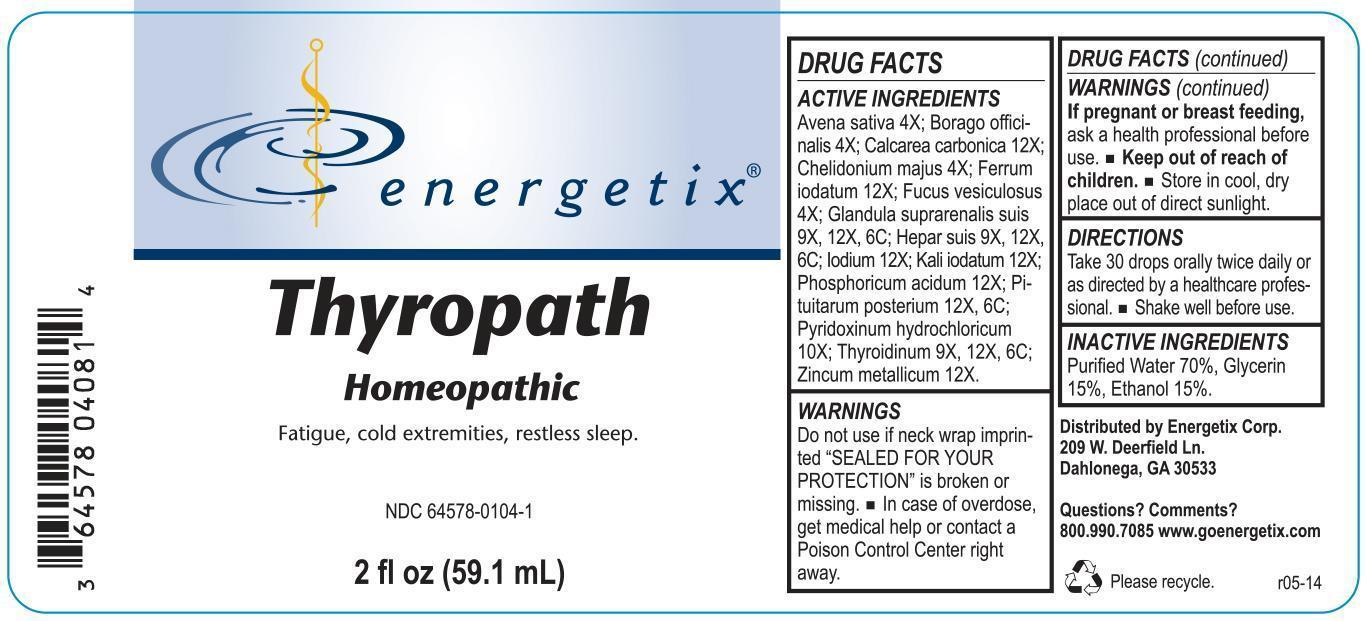 DRUG LABEL: Thyropath
NDC: 64578-0104 | Form: LIQUID
Manufacturer: Energetix Corp
Category: homeopathic | Type: HUMAN OTC DRUG LABEL
Date: 20140506

ACTIVE INGREDIENTS: AVENA SATIVA FLOWERING TOP 4 [hp_X]/59.1 mL; BORAGE 4 [hp_X]/59.1 mL; OYSTER SHELL CALCIUM CARBONATE, CRUDE 12 [hp_X]/59.1 mL; CHELIDONIUM MAJUS 4 [hp_X]/59.1 mL; FERROUS IODIDE 12 [hp_X]/59.1 mL; FUCUS VESICULOSUS 4 [hp_X]/59.1 mL; SUS SCROFA ADRENAL GLAND 9 [hp_X]/59.1 mL; PORK LIVER 9 [hp_X]/59.1 mL; IODINE 12 [hp_X]/59.1 mL; POTASSIUM IODIDE 12 [hp_X]/59.1 mL; PHOSPHORIC ACID 12 [hp_X]/59.1 mL; SUS SCROFA PITUITARY GLAND 12 [hp_X]/59.1 mL; PYRIDOXINE HYDROCHLORIDE 10 [hp_X]/59.1 mL; THYROID, UNSPECIFIED 9 [hp_X]/59.1 mL; ZINC 12 [hp_X]/59.1 mL
INACTIVE INGREDIENTS: WATER 41.359 mL/59.1 mL; GLYCERIN 8.862 mL/59.1 mL; ALCOHOL 8.862 mL/59.1 mL

Thyropath

ACTIVE INGREDIENT

Avena sativa 4X; Borago officinalis 4X; Calcarea carbonica 12X; Chelidonium majus 4X; Ferrum iodatum 12X; Fucus vesiculosus 4X; Glandula suprarenalis suis 9X, 12X, 6C; Hepar suis 9X, 12X, 6C; Iodium 12X; Kali iodatum 12X; Phosphoricum acidum 12X; Pituitarum posterium 12X, 6C; Pyridoxinum hydrochloricum 10X; Thyroidinum 9X, 12X, 6C; Zincum metallicum 12X

Do not use if neck wrap imprinted "SEALED FOR YOUR PROTECTION" is broken or missing.

OVERDOSAGE

In case of overdose, get medical help or contact a Poison Control Center right away.

PREGNANCY OR BREAST FEEDING

If pregnant or breast feeding, ask a health professional before use.

Keep out of reach of children.

STORAGE AND HANDLING

Store in cool, dry place out of direct sunlight.

Questions? Comments?
800.990.7085 www.goenergetix.com

PURPOSE

Fatigue, cold extremities, restless sleep.

INACTIVE INGREDIENT

Purified Water 70%, Glycerin 15%, Ethanol 15%.

DOSAGE AND ADMINISTRATION

Take 30 drops orally twice daily or as directed by a healthcare professional. Shake well before use.

INDICATIONS AND USAGE

Fatigue, cold extremities, restless sleep.